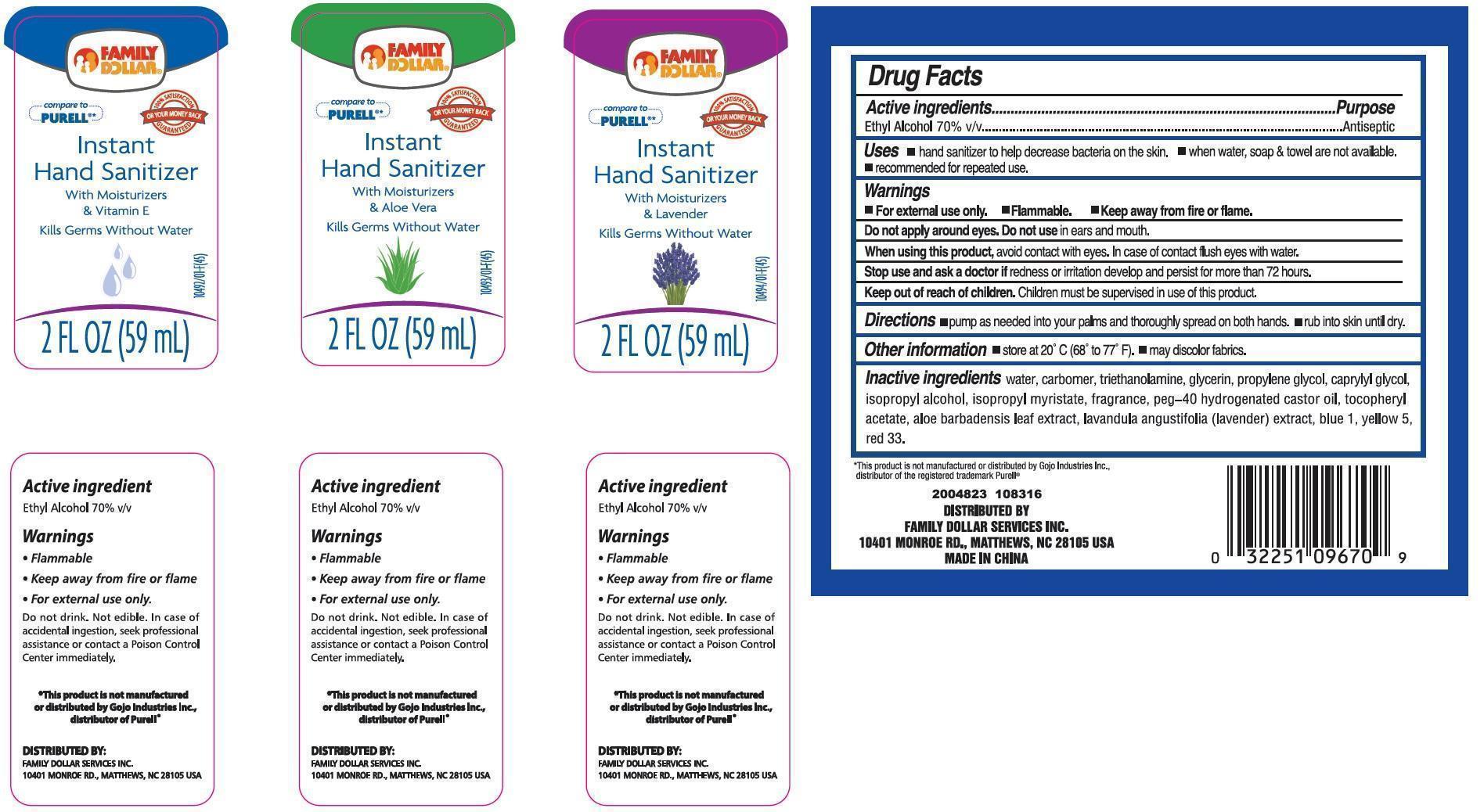 DRUG LABEL: 3 Pack Family Dollar instant Hand Sanitizers
NDC: 40104-360 | Form: KIT | Route: TOPICAL
Manufacturer: Ningbo Pulisi Daily Chemical Products Co., Ltd.
Category: otc | Type: HUMAN OTC DRUG LABEL
Date: 20141128

ACTIVE INGREDIENTS: ALCOHOL 70 mL/100 mL; ALCOHOL 70 mL/100 mL; ALCOHOL 70 mL/100 mL
INACTIVE INGREDIENTS: water; PROPYLENE GLYCOL; ALOE VERA LEAF; CARBOMER 934; GLYCERIN; .ALPHA.-TOCOPHEROL ACETATE, D-; D&C RED NO. 33; water; PROPYLENE GLYCOL; ALOE VERA LEAF; CARBOMER 934; GLYCERIN; .ALPHA.-TOCOPHEROL ACETATE, D-; water; PROPYLENE GLYCOL; ALOE VERA LEAF; CARBOMER 934; GLYCERIN; .ALPHA.-TOCOPHEROL ACETATE, D-; FD&C BLUE NO. 1

Drug facts

Active ingredient Purpose

Active ingredient Purpose

Ethyl Alcohol 70% ... Antiseptic

PURPOSE

- hand sanitizer to help decrease bacteria on the skin.
- when water, soap and towel are not available
- recommended for repeat use.

Warnings

Children must be supervised in use of this product.

WARNINGS

- For External use only
- Flammable
- keep away from fire or flame

Do not apply around eyes, avoid contact with eyes, in case of contact flush eyes with water.

Stop use and ask a doctor if redness and irritation developand persists for more than 72 hours.

Directions

Pump as needed into your palms and thoroughly spread on both hands.

Rub into skin until dry.

DOSAGE AND ADMINISTRATION

pump as needed into your palms and thoroughly spread on both hands.

rub into skin until dry.

Other Information:

store at 20°C - 25°C (68°F to 77°F). may discolor fabrics.

INACTIVE INGREDIENT

Water, Carbomer, Glycerin, Propylene Glycol, Triethanolamine, Aloe Barbadensis Leaf extract, lavandula angustifolia (lavender) extract, Tocopheryl Acetate, Fragrance, peg-40 hydrgenated castor oil, Yellow 5, Yellow 6, Blue 1, Red 33, Red 40